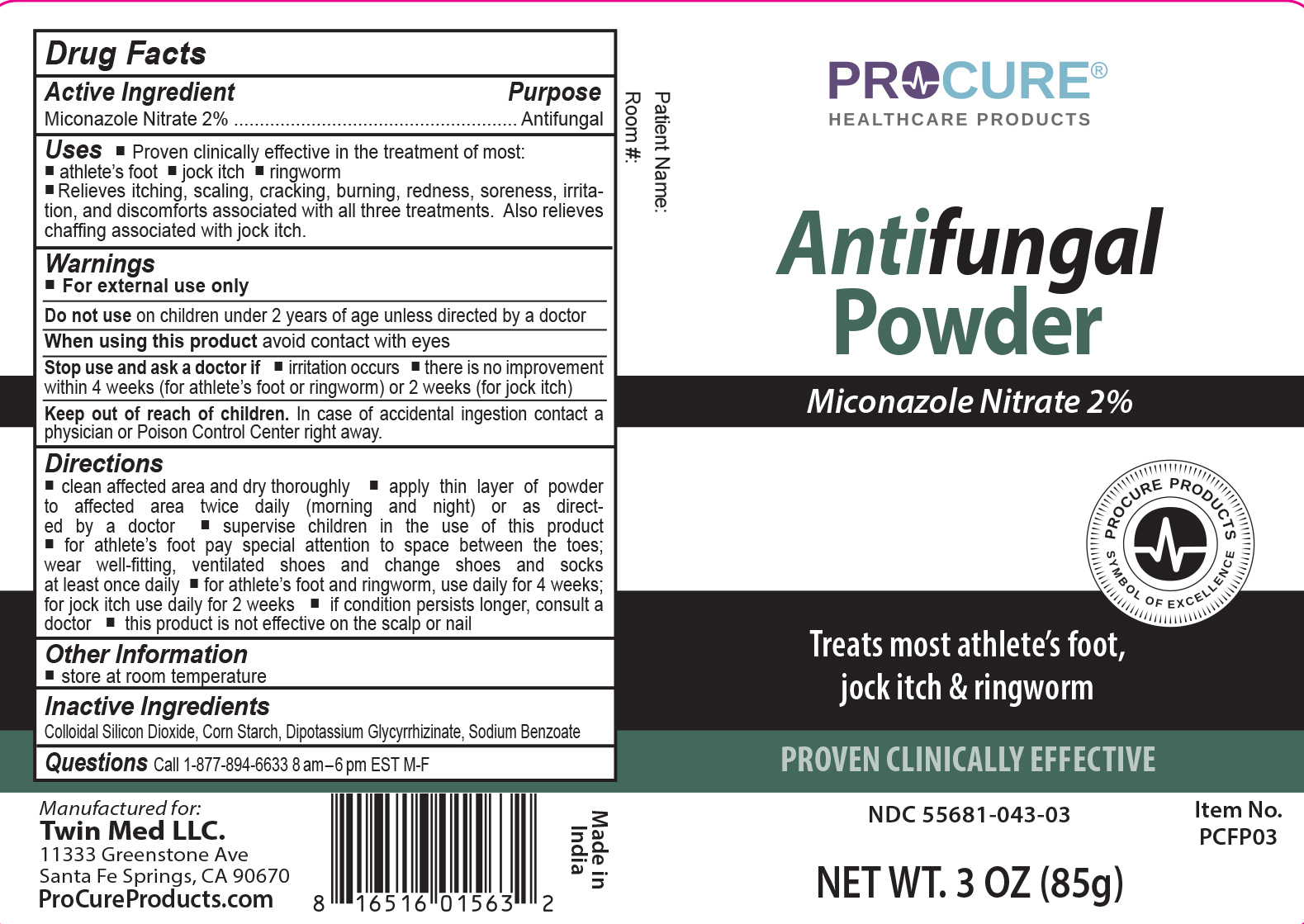 DRUG LABEL: ProCure Antifungal
NDC: 55681-043 | Form: POWDER
Manufacturer: Twin Med LLC
Category: otc | Type: HUMAN OTC DRUG LABEL
Date: 20251201

ACTIVE INGREDIENTS: MICONAZOLE NITRATE 2 g/100 g
INACTIVE INGREDIENTS: STARCH, CORN; SODIUM BENZOATE; GLYCYRRHIZINATE DIPOTASSIUM; SILICON DIOXIDE

Active Ingredient

Mconazole Nitrate 2%

Purpose

Antifungal

Uses

- Proven clinically effective in the treatment of most athlete’s foot, jock itch and ringworm
- Relieves itching, scaling, cracking, burning, redness, soreness, irritation, and discomforts associated with all three treatments. Also relieves chaffing associated with jock itch.

Warnings

For external use only

Do not use on children under 2 years of age unless directed by a doctor

When using this product avoid contact with eyes

Stop using and ask a doctor if

- irritation occurs
- there is no improvement within 4 weeks (for athlete’s foot or ringworm) or 2 weeks (for jock itch)

Keep out of reach of Children. In case of accidental ingestion, contact a physician or Poison Control Center right away.

Directions

- clean affected area and dry thoroughly
- apply thin layer of powder to affected area twice daily (morning and night) or as directed by a doctor
- supervise children in the use of this product
- for athlete’s foot pay special attention to space between the toes; wear well-fitting, ventilated shoes and change shoes and socks at least once daily.
- for athlete’s foot and ringworm, use daily for 4 weeks; for jock itch use daily for 2 weeks
- if condition persists longer, consult a doctor
- this product is not effective on the scalp or nails

Inactive Ingredients

Inactive Ingredients: Colloidal Silicon Dioxide, Corn Starch, Dipotassium Glycyrrhizinate, Sodium Benzoate